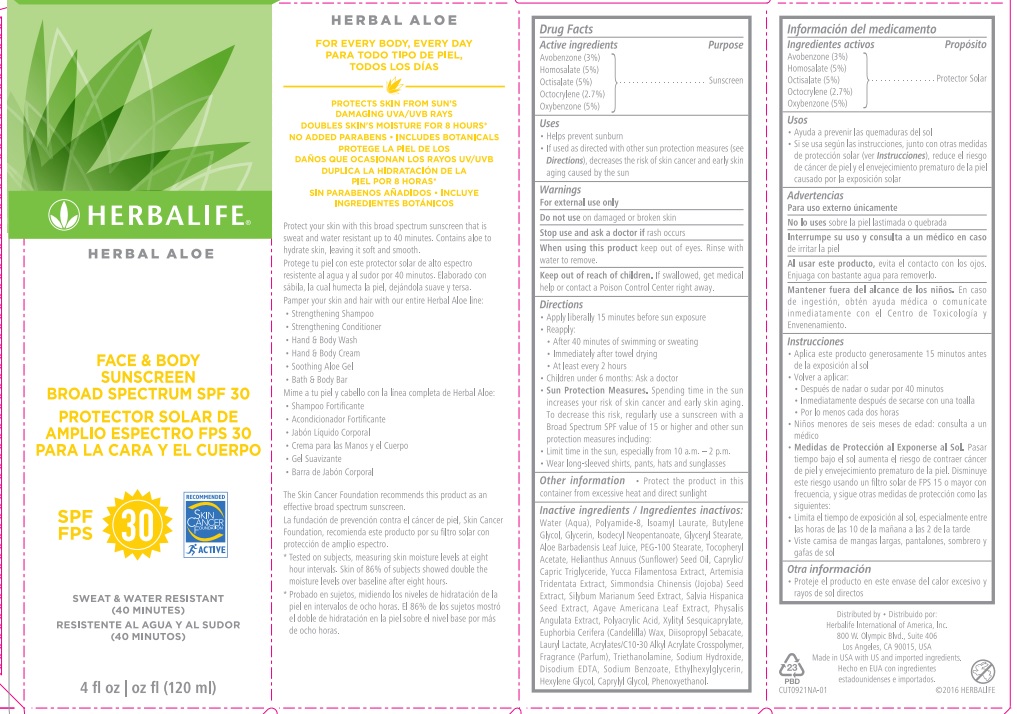 DRUG LABEL: Herbal Aloe Face and Body SPF 30
NDC: 51785-921 | Form: CREAM
Manufacturer: Herbalife International of America, Inc.
Category: otc | Type: HUMAN OTC DRUG LABEL
Date: 20191219

ACTIVE INGREDIENTS: OXYBENZONE 7.2 g/1 mL; HOMOSALATE 6.24 g/1 mL; OCTISALATE 6.06 g/1 mL; AVOBENZONE 3.8844 g/1 mL; OCTOCRYLENE 3.4 g/1 mL
INACTIVE INGREDIENTS: GLYCERYL MONOSTEARATE; PEG-100 STEARATE; CARBOMER INTERPOLYMER TYPE A (ALLYL SUCROSE CROSSLINKED); GLYCERIN; SODIUM BENZOATE; YUCCA FILAMENTOSA; SIMMONDSIA CHINENSIS SEED; CHIA SEED; CAPRYLYL GLYCOL; ARTEMISIA TRIDENTATA TOP OIL; NEOPENTYL GLYCOL; EDETATE DISODIUM; POLYAMIDE-8 (4500 MW); AGAVE AMERICANA LEAF; PHYSALIS ANGULATA; POLYACRYLIC ACID (250000 MW); TROLAMINE; .ALPHA.-TOCOPHEROL ACETATE; ALOE VERA LEAF; PHENOXYETHANOL; LAURYL LACTATE; MEDIUM-CHAIN TRIGLYCERIDES; SUNFLOWER OIL; CANDELILLA WAX; BUTYLENE GLYCOL; WATER; MILK THISTLE; ETHYLHEXYLGLYCERIN; ISODECYL NEOPENTANOATE; DIISOPROPYL SEBACATE; ISOAMYL LAURATE; HEXYLENE GLYCOL; XYLITOL; SODIUM HYDROXIDE

Herbalife Herbal Aloe Face and Body Sunscreen SPF 30

Drug Facts

Purpose

Sunscreen

Active ingredients

Avobenzone (3%)

Homosalate (5%)

Octisalate (5%)

Octocrylene (2.7%)

Oxybenzone (5%)

Uses

• Helps prevent sunburn

• If used as directed with other sun protection measures (see Directions), decreases the risk of skin cancer and early skin aging caused by the sun

Warnings

For external use only

Do not use on damaged or broken skin

Stop use and ask a doctor if rash occurs

When using this product keep out of eyes. Rinse with water to remove.

Keep out of reach of children. If swallowed, get medical help or contact a Poison Control Center right away.

Directions

• Apply liberally 15 minutes before sun exposure

• Reapply:

• After 40 minutes of swimming or sweating

• Immediately after towel drying

• At least every 2 hours

• Children under 6 months: Ask a doctor

• Sun Protection Measures. Spending time in the sun increases your risk of skin cancer and early skin aging. To decrease this risk, regularly use a sunscreen with a Broad Spectrum SPF value of 15 or higher and other sun protection measures including:

• Limit time in the sun, especially from 10 a.m. – 2 p.m.

• Wear long-sleeved shirts, pants, hats and sunglasses

Other information

• Protect the product in this container from excessive heat and direct sunlight

INACTIVE INGREDIENT

Inactive ingredients: Water (Aqua), Polyamide-8, Isoamyl Laurate, Butylene Glycol, Glycerin, Isodecyl Neopentanoate, Glyceryl Stearate, Aloe Barbadensis Leaf Juice, PEG-100 Stearate, Tocopheryl Acetate, Helianthus Annuus (Sunflower) Seed Oil, Caprylic/ Capric Triglyceride, Yucca Filamentosa Extract, Artemisia Tridentata Extract, Simmondsia Chinensis (Jojoba) Seed Extract, Silybum Marianum Seed Extract, Salvia Hispanica Seed Extract, Agave Americana Leaf Extract, Physalis Angulata Extract, Polyacrylic Acid, Xylityl Sesquicaprylate, Euphorbia Cerifera (Candelilla) Wax, Diisopropyl Sebacate, Lauryl Lactate, Acrylates/C10-30 Alkyl Acrylate Crosspolymer, Fragrance (Parfum), Triethanolamine, Sodium Hydroxide, Disodium EDTA, Sodium Benzoate, Ethylhexylglycerin, Hexylene Glycol, Caprylyl Glycol, Phenoxyethanol.

Distributed by:

Herbalife International of America, Inc.

800 W. Olympic Blvd., Suite 406

Los Angeles, CA 90015, USA

Made in USA with US and imported ingredients.

©2016 HERBALIFE

FOR EVERY BODY, EVERY DAY

PROTECTS SKIN FROM SUN’S

DAMAGING UVA/UVB RAYS

DOUBLES SKIN'S MOISTURE FOR 8 HOURS*

NO ADDED PARABENS • INCLUDES BOTANICALS

Protect your skin with this broad spectrum sunscreen that is sweat and water resistant up to 40 minutes. Contains aloe to hydrate skin, leaving it soft and smooth.

Pamper your skin and hair with our entire Herbal Aloe line:

• Strengthening Shampoo

• Strengthening Conditioner

• Hand & Body Wash

• Hand & Body Cream

• Soothing Aloe Gel

• Bath & Body Bar

The Skin Cancer Foundation recommends this product as an effective broad spectrum sunscreen.

* Tested on subjects, measuring skin moisture levels at eight hour intervals. Skin of 86% of subjects showed double the moisture levels over baseline after eight hours.

PACKAGE LABEL

HERBALIFE

HERBAL ALOE

FACE & BODY

SUNSCREEN

BROAD SPECTRUM SPF 30

SPF 30

SWEAT & WATER RESISTANT

(40 MINUTES)

4 fl oz (120 ml)